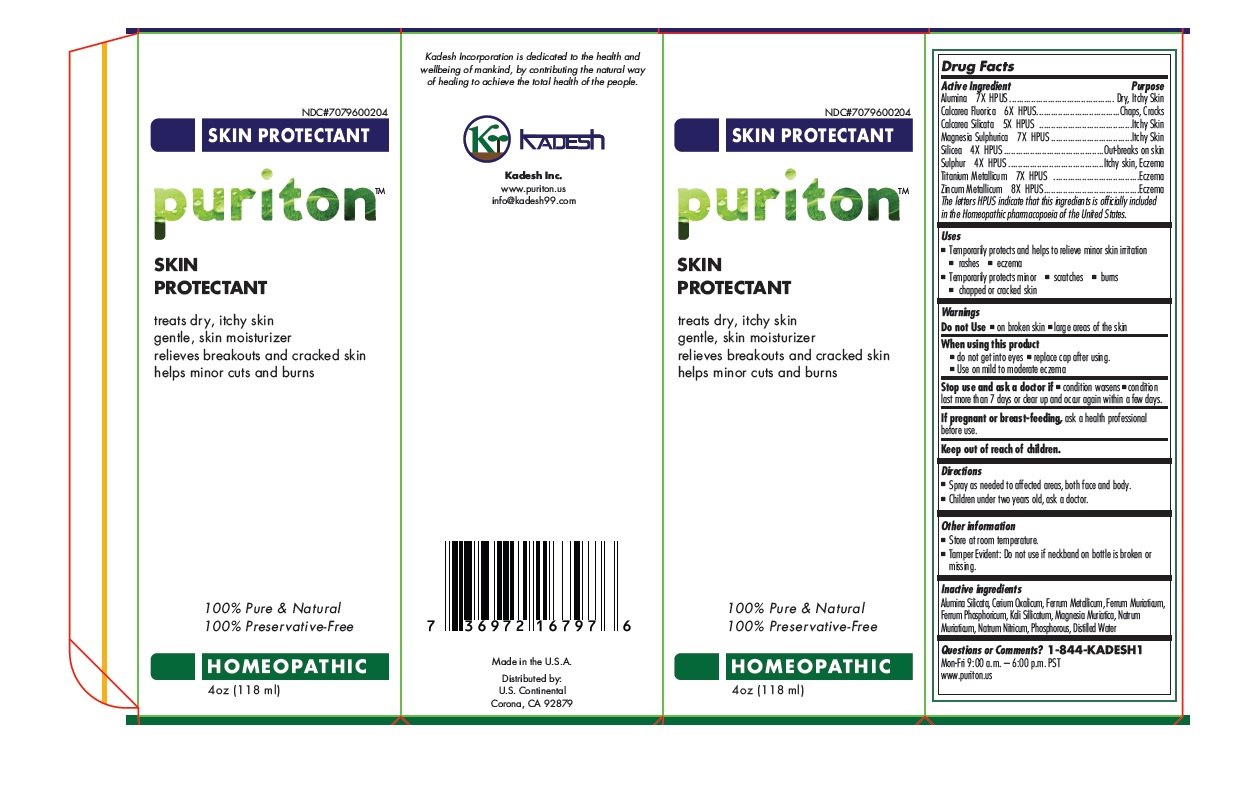 DRUG LABEL: Puriton SKIN PROTECTANT HOMEOPATHIC
NDC: 70796-002 | Form: SPRAY
Manufacturer: Kadesh, Inc.
Category: homeopathic | Type: HUMAN OTC DRUG LABEL
Date: 20160806

ACTIVE INGREDIENTS: ALUMINUM OXIDE 7 [hp_X]/118 mL; CALCIUM FLUORIDE 6 [hp_X]/118 mL; CALCIUM SILICATE 5 [hp_X]/118 mL; MAGNESIUM SULFATE HEPTAHYDRATE 7 [hp_X]/118 mL; SILICON DIOXIDE 4 [hp_X]/118 mL; SULFUR 4 [hp_X]/118 mL; TITANIUM 7 [hp_X]/118 mL; ZINC 8 [hp_X]/118 mL
INACTIVE INGREDIENTS: KAOLIN; CEROUS OXALATE NONAHYDRATE; IRON; FERRIC CHLORIDE HEXAHYDRATE; FERROSOFERRIC PHOSPHATE; POTASSIUM SILICATE; MAGNESIUM CHLORIDE; SODIUM CHLORIDE; SODIUM NITRATE; PHOSPHORUS; WATER

puriton SKIN PROTECTANT HOMEOPATHIC

Active ingredient

Alumina 7X HPUS
Calcarea Fluorica 6X HPUS
Calcarea Silicata 5X HPUS
Magnesia Sulphurica 7X HPUS
Silicea 4X HPUS
Sulphur 4X HPUS
Titanium Metallicum 7X HPUS
Zincum Metallicum 8X HPUS

The letters HPUS indicate that this ingredients is officially included in the Homoeopathic pharmacopoeia of the United States.

Purpose

Dry, Itchy skin
Chaps, Cracks
Itchy Skin
Itchy Skin
Out-breaks on skin
Itchy skin, Eczema
Eczema
Eczema

Uses

• Temporarily protects and helps to relieve minor skin irritation

• rashes • eczema
• Temporarily protects minor • scratches • burns

• chapped or cracked skin

Warnings

Do not Use • on broken skin • large areas of the skin

When using this product

• do not get into eyes • replace cap after using

• Use on mild to moderate eczema

Stop use and ask a doctor if • condition worsens • condition last more than 7 days or clear up and occur again within a few days

If pregnant or breast-feeding, ask a health professional before use.

Keep out of reach of children.

Directions

• Spray as needed to affected areas, both face and body.
• Children under two years old, ask a doctor.

Inactive ingredients

Alumina Silicata, Cerium Oxalicum, Ferrum Metallicum, Ferrum Muriaticum, Ferrum Phosphoricum, Kali Silicatum, Magnesia Muriatica, Natrum Muriaticum, Natrum Nitricum, Phosphorous, Distilled Water

Other information

• Store at room temperature.
• Tamper Evident: Do not use if neckband on bottle is broken or missing.

Questions or Comments? 1-844-KADESH1
Mon - Fri. 9.00 a.m. - 6.00 p.m. PST
www.puriton.us

treats dry, itchy skin

gentle, skin moisturizer

relieves breakouts and cracked skin

helps minor cuts and burns

100% Pure & Natural
100% Preservative-Free

Made in the U.S.A

Distributed by:
U.S. Continental

Corona, CA 92879
info@kadesh99.com